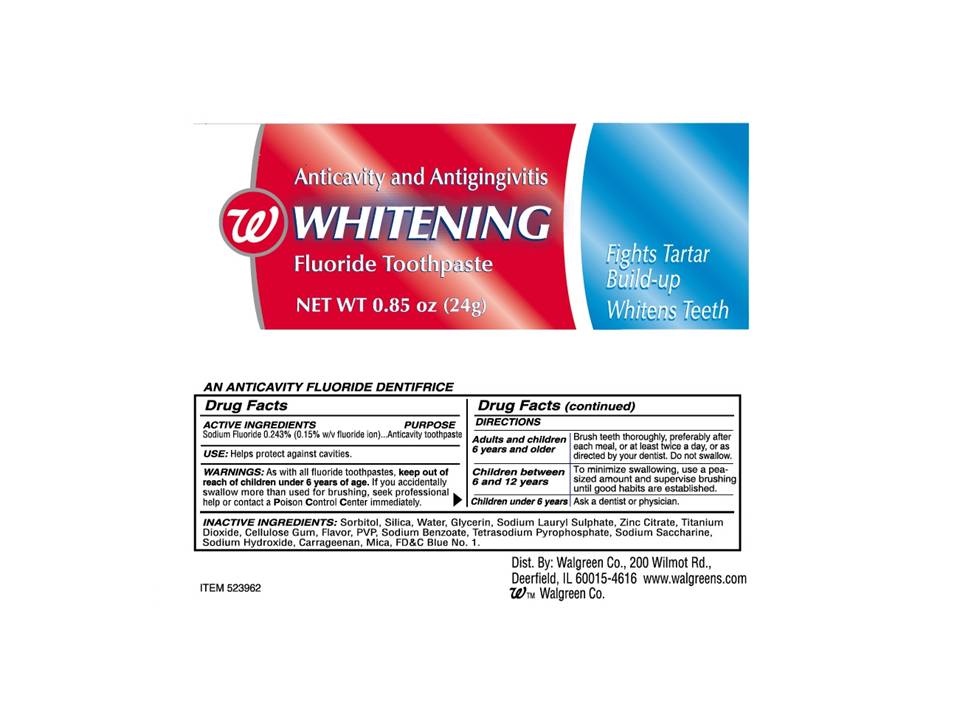 DRUG LABEL: Walgreens Anticavity and Antigingivitis Whitening 
NDC: 0363-9529 | Form: PASTE, DENTIFRICE
Manufacturer: Walgreen
Category: otc | Type: HUMAN OTC DRUG LABEL
Date: 20111116

ACTIVE INGREDIENTS: Sodium Fluoride 2.43 mg/1 g
INACTIVE INGREDIENTS: Sorbitol; SILICON DIOXIDE; Water; Glycerin; SODIUM LAURYL SULFATE; Zinc Citrate; Titanium Dioxide; CROSCARMELLOSE SODIUM; SODIUM BENZOATE; SODIUM PYROPHOSPHATE; SACCHARIN SODIUM; SODIUM HYDROXIDE; Carrageenan; FD&C BLUE NO. 1

Walgreens Anticavity and Antigingivitis Whitening Fluoride Toothpaste

Active Ingredient

Sodium Fluoride 0.234% (0.15% w/v fluoride ion..........................Anticavity toothpaste

WARNINGS

As with all fluoride toothpastes, keep out of reach of children under 6 years of age. If you accidentally swallow more than used for brushing, seek professional help or contact the Poison Control Center immediately.

Directions

Adults and children 6 years or older | Brush Teeth throughly, preferably after each meal, or at least twice a day, or as directed by your dentist. Do not swallow.
Children between 6 years and 12 years | To minimize swallowing, use a pea sized amount and supervise brushing until good habits are established.
Children under 6 years | Ask a dentist or physician,

Inactive Ingredients

Sorbitol, Silica, Water, Glycerin, Sodium Laurel Sulphate, Zinc Citrate, Titanium Dioxide, Cellulose Gum, Flavor, PVP, Sodium Benzoate, Tetrasodium Pyrophosphate, Sodium Saccharine, Sodium Hydroxide, Carrageenan, Mica, FDC Blue No. 1.

USE

Helps protect against cavities.